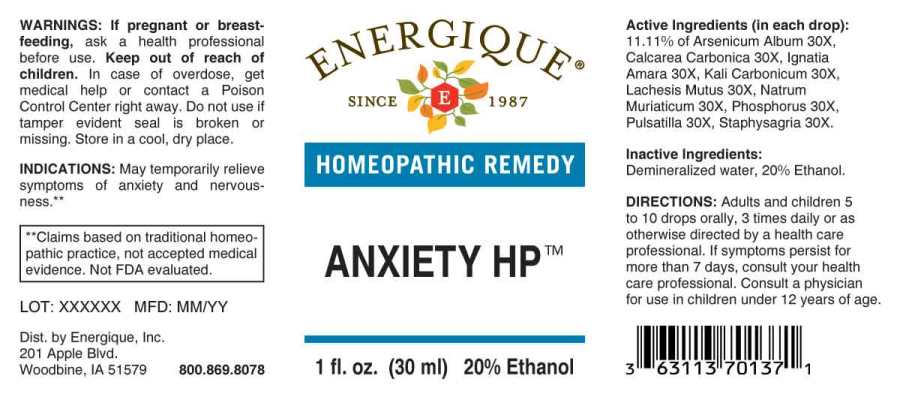 DRUG LABEL: Anxiety
NDC: 44911-0511 | Form: LIQUID
Manufacturer: Energique, Inc.
Category: homeopathic | Type: HUMAN OTC DRUG LABEL
Date: 20230614

ACTIVE INGREDIENTS: ARSENIC TRIOXIDE 30 [hp_X]/1 mL; OYSTER SHELL CALCIUM CARBONATE, CRUDE 30 [hp_X]/1 mL; STRYCHNOS IGNATII SEED 30 [hp_X]/1 mL; POTASSIUM CARBONATE 30 [hp_X]/1 mL; LACHESIS MUTA VENOM 30 [hp_X]/1 mL; SODIUM CHLORIDE 30 [hp_X]/1 mL; PHOSPHORUS 30 [hp_X]/1 mL; PULSATILLA PRATENSIS WHOLE 30 [hp_X]/1 mL; DELPHINIUM STAPHISAGRIA SEED 30 [hp_X]/1 mL
INACTIVE INGREDIENTS: WATER; ALCOHOL

Drug Facts:

ACTIVE INGREDIENTS:

(in each drop): 11.11% of Arsenicum Album 30X, Calcarea Carbonica 30X, Ignatia Amara 30X, Kali Carbonicum 30X, Lachesis Mutus 30X, Natrum Muriaticum 30X, Phosphorus 30X, Pulsatilla (Pratensis) 30X, Staphysagria 30X.

INDICATIONS:

May temporarily relieve symptoms of anxiety and nervousness. **

**Claims based on traditional homeopathic practice, not accepted medical evidence. Not FDA evaluated.

WARNINGS:

If pregnant or breast-feeding, ask a health professional before use.

Keep out of reach of children. In case of overdose, get medical help or contact a Poison Control Center right away.

Do not use if tamper evident seal is broken or missing. Store in a cool, dry place.

Keep out of reach of children. In case of overdose, get medical help or contact a Poison Control Center right away.

DIRECTIONS:

Adults and children 5 to 10 drops orally, 3 times daily or as otherwise directed by a health care professional. If symptoms persist for more than 7 days, consult your health care professional. Consult a physician for use in children under 12 years of age.

INDICATIONS:

May temporarily relieve symptoms of anxiety and nervousness. **

**Claims based on traditional homeopathic practice, not accepted medical evidence. Not FDA evaluated.

INACTIVE INGREDIENTS:

Demineralized water, 20% Ethanol.

QUESTIONS:

Dist. by Energique, Inc.

201 Apple Blvd.

Woodbine, IA 51579

800-869-8078

PACKAGE LABEL DISPLAY:

ENERGIQUE

SINCE 1987

HOMOEPATHIC REMEDY

ANXIETY HP

1 fl. oz. (30 ml)